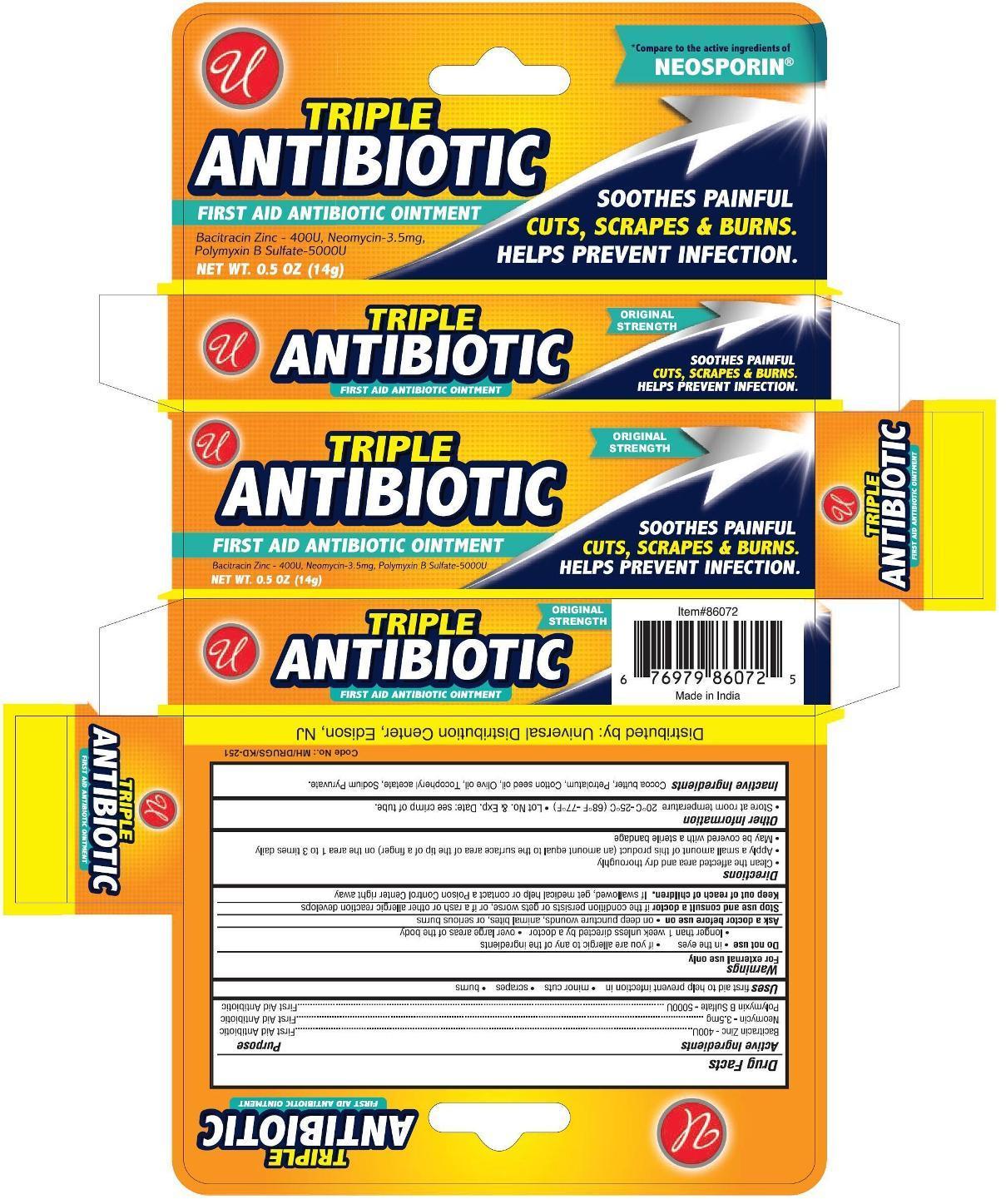 DRUG LABEL: Triple Antibiotic First Aid
NDC: 52000-019 | Form: OINTMENT
Manufacturer: Universal Distribution Center LLC
Category: otc | Type: HUMAN OTC DRUG LABEL
Date: 20241017

ACTIVE INGREDIENTS: BACITRACIN ZINC 400 [USP'U]/1 g; NEOMYCIN SULFATE 3.5 mg/1 g; POLYMYXIN B SULFATE 5000 [USP'U]/1 g
INACTIVE INGREDIENTS: COCOA BUTTER; PETROLATUM; COTTONSEED OIL; OLIVE OIL; .ALPHA.-TOCOPHEROL ACETATE; SODIUM PYRUVATE

Triple Antibiotic First Aid Ointment

Active Ingredients

Bacitracin Zinc 400U

Neomycin 3.5 mg

Polymyxin B Sulfate 5000U

Purpose

First Aid Antibiotic

Uses

first aid to help prevent infection in

- minor cuts
- scrapes
- burns

Warnings

For external use only

Do not use

- in the eyes
- if you are allergic to any of the ingredients
- longer than 1 week unless directed by a doctor
- over large areas of the body

Ask a doctor before use on

- on deep puncture wounds, animal bites, or serious burns

Stop use and consult a doctor if the condition persists or gets worse, or if a rash or other allergic reaction develops

Keep out of reach of children. If swallowed, get medical help or contact a Poison Control Center right away.

Directions

- Clean the affected area and dry thoroughly
- Apply a small amount of this product (an amount equal to the surface area of the tip of a finger) on the area 1 to 3 times daily
- May be covered with a sterile bandage

Other Information

- Store at room temperature 20°C to 25°C (68°F to 77°C)
- Lot No. & Exp. Date: see crimp of tube

Inactive Ingredients

Cocoa butter, Petrolatum, Cotton seed oil, Olive oil, Tocopheryl acetate, Sodium pyruvate.

PACKAGE LABEL

PRINCIPAL DISPLAY PANEL

Triple Antibiotic First Aid Ointment

NET WT 0.5 OZ (14 g)